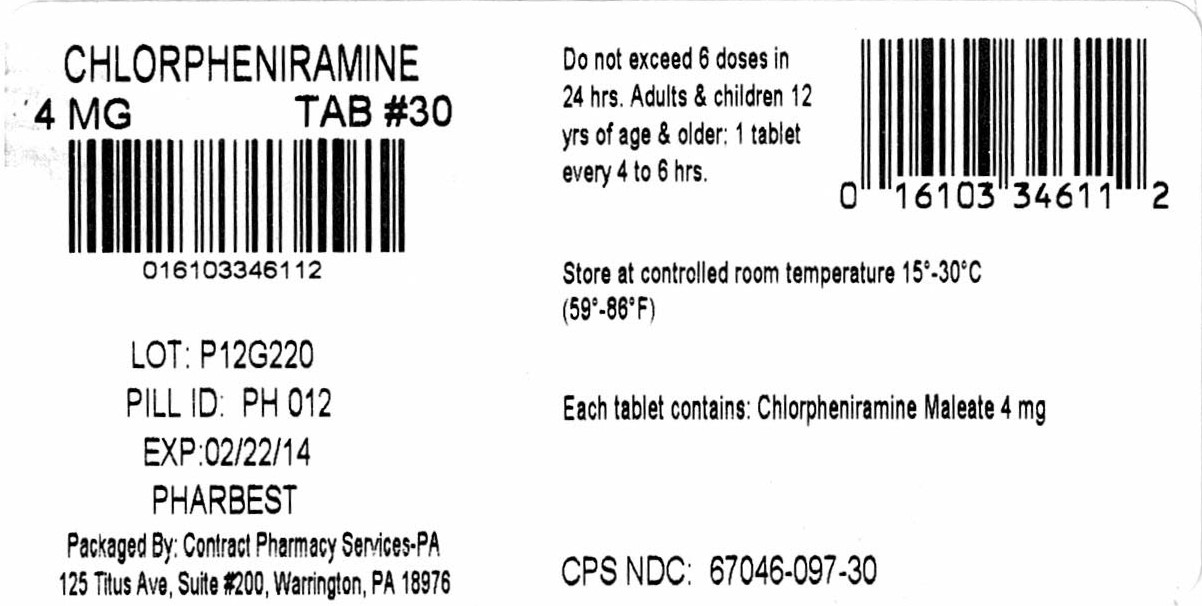 DRUG LABEL: Chlorpheniramine Maleate
NDC: 67046-097 | Form: TABLET
Manufacturer: Contract Pharmacy Services-PA
Category: otc | Type: HUMAN OTC DRUG LABEL
Date: 20170919

ACTIVE INGREDIENTS: CHLORPHENIRAMINE MALEATE 4 mg/1 1
INACTIVE INGREDIENTS: STARCH, CORN; CROSCARMELLOSE SODIUM; D&C YELLOW NO. 10; ANHYDROUS DIBASIC CALCIUM PHOSPHATE; MAGNESIUM STEARATE; CELLULOSE, MICROCRYSTALLINE; SILICON DIOXIDE

Drug Facts 097

Active ingredient(in each tablet)

Chlorpheniramine Maleate 4 mg

Purpose

Antihistamine

Uses

Temporarily relieves these symptoms due to hay fever or other upper respiratory allergies:

- runny nose
- itchy nose or throat
- itchy watery eyes
- sneezing

Ask a doctor before use if you have,

- a breathing problem such as emphysema or chronic bronchitis
- glaucoma
- trouble urinating due to enlarged prostate gland

Ask a doctor or pharmacist before use if you

are taking sedatives or tranquilizers

When using this product

- excitability may occur, especially in children
- drowsiness may occur
- avoid alcoholic beverages
- alcohol, sedatives and tranquilizers may increase drowsiness
- use caution when driving a motor vehicle or operating machinery

If pregnant or breast feeding,

ask a health professional before use

Keep out of reach of children.

In case of overdose, get medical help or contact a poison control center right away.

Directions

adults and children 12 years of age and older | one tablet 4 to 6 hours, not to exceed 6 tablets in 24 hours
children 6 to under 12 years of age | 1/2 tablet every 4 to 6 hours, not to exceed 3 whole tablets in 24 hours
children under 6 years of age | consult a physician

Other information

- Tamper Evident: Do not Use If Safety Seal Under Cap Is Broken Or Missing
- store at controlled room temperature 15o-25oC (59o-77oF)
- protect from excessive moisture

Questions:

To Report Adverse Drug Events Call 800-687-0176.